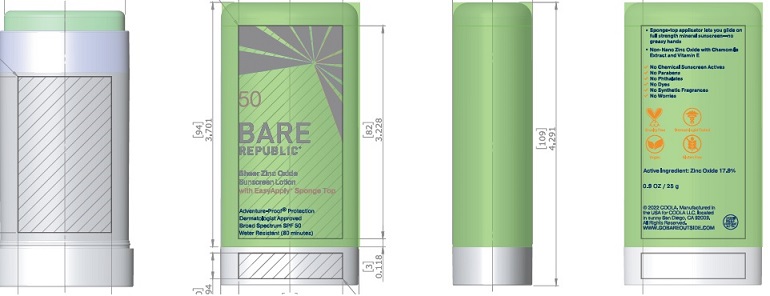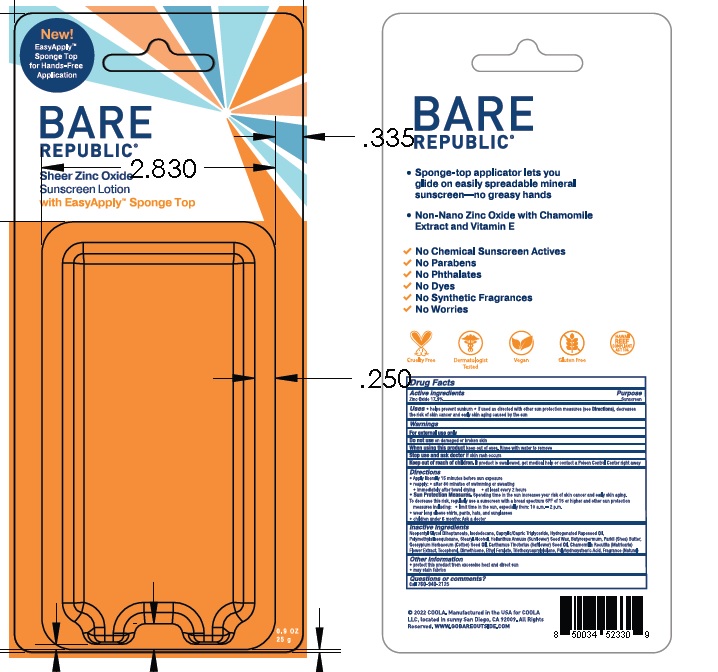 DRUG LABEL: Bare Republic Mineral SPF 50
NDC: 79753-069 | Form: STICK
Manufacturer: COOLA LLC
Category: otc | Type: HUMAN OTC DRUG LABEL
Date: 20241227

ACTIVE INGREDIENTS: ZINC OXIDE 17.9 g/100 g
INACTIVE INGREDIENTS: NEOPENTYL GLYCOL DIHEPTANOATE; ISODODECANE; MEDIUM-CHAIN TRIGLYCERIDES; HYDROGENATED RAPESEED OIL; POLYMETHYLSILSESQUIOXANE (11 MICRONS); STEARYL ALCOHOL; HELIANTHUS ANNUUS SEED WAX; DIMETHICONE; ETHYL FERULATE; TRIETHOXYCAPRYLYLSILANE; POLYHYDROXYSTEARIC ACID (2300 MW); TOCOPHEROL; SHEA BUTTER; LEVANT COTTONSEED OIL; SAFFLOWER OIL; CHAMOMILE; .ALPHA.-TOCOPHEROL ACETATE

Bare Republic Sheer Zinc Oxide Sunscreen Lotion

Drug Facts

Active Ingredients

Zinc Oxide 17.9%

Purpose

Suncreen

Uses

- helps prevent sunburn • if used as directed with other sun protection measures (see Directions), decreases

the risk of skin cancer and early skin aging caused by the sun

Warnings

For external use only

Do not use on damaged or broken skin

When using this product keep out of eyes. Rinse with water to remove.

Stop use and ask doctor if skin rash occurs

Keep out of reach of children. If product is swallowed, get medical help or contact a Poison Control Center right away.

Directions
● apply liberally 15 minutes before sun exposure.
● reapply: ● after 80 minutes of swimming or sweating
● immediately after towel drying ● at least every 2 hours
● Sun Protection Measures. Spending time in the sun increases your risk of skin cancer and early skin aging.
To decrease this risk, regularly use a sunscreen with a broad spectrum SPF of 15 or higher and other sun protection
measures including: ● limit time in the sun, especially from: 10 a.m. - 2 p.m.
● wear long-sleeve shirts, pants, hats, and sunglasses
●Children under 6 months: Ask a doctor

Inactive Ingredients
Neopentyl Glycol Diheptanoate, Isododecane, Caprylic/Capric Triglyceride, Hydrogenated Rapeseed Oil,
Polymethylsilsesquioxane, Stearyl Alcohol, Helianthus Annuus (Sunflower) Seed Wax, Butyrospermum Parkii (Shea) Butter,
Gossypium Herbaceum (Cotton) Seed Oil, Carthamus Tinctorius (Safflower) Seed Oil, Chamomilla Recutita (Matricaria)
Flower Extract, Tocopherol, Dimethicone, Ethyl Ferulate, Triethoxycaprylylsilane, Polyhydroxystearic Acid, Fragrance (Natural)

Other information

- protect this product from excessive heat and direct sun
- may stain fabrics

Questions or comments?
Call 760-940-2125

COOLA Label

BARE

REPUBLIC®

Sheer Zinc Oxide

Sunscreen Lotion

0.9 OZ

25 g

©2022 COOLA. Manufactured in the USA for COOLA

LLC, located in sunny San Diego, CA 92009. All Rights

Reserved. WWW.GOBAREOUTSIDE.COM

res